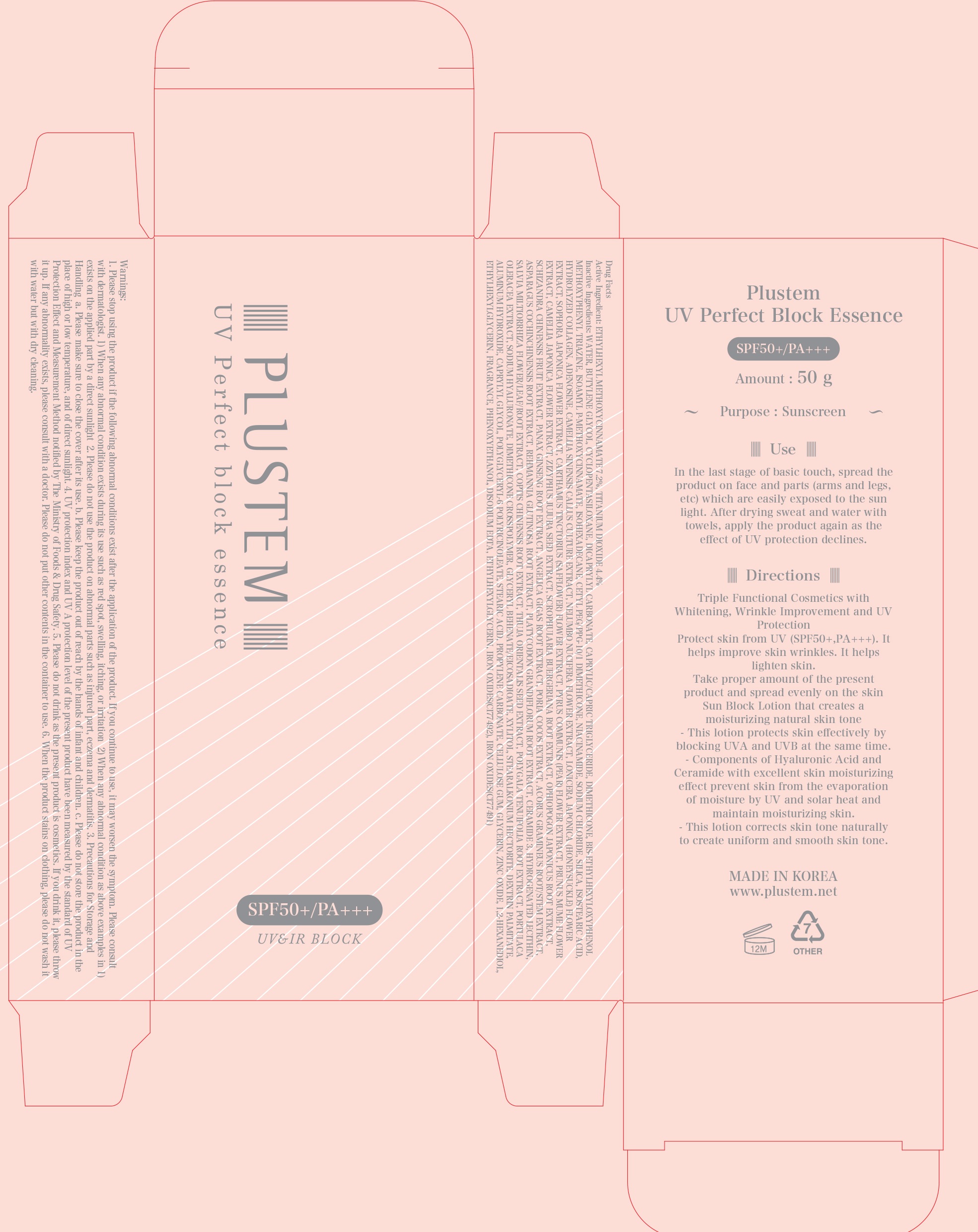 DRUG LABEL: Plustem UV Perfect Block Essence
NDC: 71060-020 | Form: CREAM
Manufacturer: ONA
Category: otc | Type: HUMAN OTC DRUG LABEL
Date: 20190124

ACTIVE INGREDIENTS: OCTINOXATE 3.6 g/50 g; TITANIUM DIOXIDE 2.2 g/50 g
INACTIVE INGREDIENTS: WATER; BUTYLENE GLYCOL

ACTIVE INGREDIENT

Active Ingredient: ETHYLHEXYL METHOXYCINNAMATE 7.2%, TITANIUM DIOXIDE 4.4%

INACTIVE INGREDIENT

Inactive Ingredients: WATER, BUTYLENE GLYCOL, CYCLOPENTASILOXANE, DICAPRYLYL CARBONATE, CAPRYLIC/CAPRIC TRIGLYCERIDE, DIMETHICONE, BIS-ETHYLHEXYLOXYPHENOL METHOXYPHENYL TRIAZINE, ISOAMYL P-METHOXYCINNAMATE, ISOHEXADECANE, CETYL PEG/PPG-10/1 DIMETHICONE, NIACINAMIDE, SODIUM CHLORIDE, SILICA, ISOSTEARIC ACID, HYDROLYZED COLLAGEN, ADENOSINE, CAMELLIA SINENSIS CALLUS CULTURE EXTRACT, NELUMBO NUCIFERA FLOWER EXTRACT, LONICERA JAPONICA (HONEYSUCKLE) FLOWER EXTRACT, SOPHORA JAPONICA FLOWER EXTRACT, CARTHAMUS TINCTORIUS (SAFFLOWER) FLOWER EXTRACT, PYRUS COMMUNIS (PEAR) FLOWER EXTRACT, PRUNUS MUME FLOWER EXTRACT, CAMELLIA JAPONICA FLOWER EXTRACT, ZIZYPHUS JUJUBA SEED EXTRACT, SCROPHULARIA BUERGERIANA ROOT EXTRACT, OPHIOPOGON JAPONICUS ROOT EXTRACT, SCHIZANDRA CHINENSIS FRUIT EXTRACT, PANAX GINSENG ROOT EXTRACT, ANGELICA GIGAS ROOT EXTRACT, PORIA COCOS EXTRACT, ACORUS GRAMINEUS ROOT/STEM EXTRACT, ASPARAGUS COCHINCHINENSIS ROOT EXTRACT, REHMANNIA GLUTINOSA ROOT EXTRACT, PLATYCODON GRANDIFLORUM ROOT EXTRACT, CERAMIDE 3, HYDROGENATED LECITHIN, SALVIA MILTIORRHIZA FLOWER/LEAF/ROOT EXTRACT, COPTIS CHINENSIS ROOT EXTRACT, THUJA ORIENTALIS SEED EXTRACT, POLYGALA TENUIFOLIA ROOT EXTRACT, PORTULACA OLERACEA EXTRACT, SODIUM HYALURONATE, DIMETHICONE CROSSPOLYMER, GLYCERYL BEHENATE/EICOSADIOATE, XYLITOL, STEARALKONIUM HECTORITE, DEXTRIN PALMITATE, ALUMINUM HYDROXIDE, CAPRYLYL GLYCOL, POLYGLYCERYL-6 POLYRICINOLEATE, STEARIC ACID, PROPYLENE CARBONATE, CELLULOSE GUM, GLYCERIN, ZINC OXIDE, 1,2-HEXANEDIOL, ETHYLHEXYLGLYCERIN, FRAGRANCE, PHENOXYETHANOL, DISODIUM EDTA, ETHYLHEXYLGLYCERIN, IRON OXIDES(CI77492), IRON OXIDES(CI77491)

PURPOSE

Purpose: Sunscreen

WARNINGS

Warnings: 1. Please stop using the product if the following abnormal conditions exist after the application of the product. If you continue to use, it may worsen the symptom. Please consult with dermatologist. 1) When any abnormal condition exists during its use such as red spot, swelling, itching, or irritation 2) When any abnormal condition as above examples in 1) exists on the applied part by a direct sunlight 2. Please do not use the product on abnormal parts such as injured part, eczema and dermatitis. 3. Precautions for Storage and Handling a. Please make sure to close the cover after its use. b. Please keep the product out of reach by the hands of infant and children. c. Please do not store the product in the place of high or low temperature, and of direct sunlight. 4. UV protection index and UV A protection level of the present product have been measured by the standard of UV Protection Effect and Measurement Method notified by The Ministry of Foods & Drug Safety. 5. Please do not drink as the present product is cosmetics. If you drink it, please throw it up. If any abnormality exists, please consult with a doctor. Please do not put other contents in the container to use. 6. When the product stains on clothing, please do not wash it with water but with dry cleaning.

DESCRIPTION

Use: In the last stage of basic touch, spread the product on face and parts (arms and legs, etc) which are easily exposed to the sun light. After drying sweat and water with towels, apply the product again as the effect of UV protection declines.

Directions: Triple Functional Cosmetics with Whitening, Wrinkle Improvement and UV Protection Protect skin from UV (SPF50+,PA+++). It helps improve skin wrinkles. It helps lighten skin. Take proper amount of the present product and spread evenly on the skin Sun Block Lotion that creates a moisturizing natural skin tone - This lotion protects skin effectively by blocking UVA and UVB at the same time. - Components of Hyaluronic Acid and Ceramide with excellent skin moisturizing effect prevent skin from the evaporation of moisture by UV and solar heat and maintain moisturizing skin. - This lotion corrects skin tone naturally to create uniform and smooth skin tone.